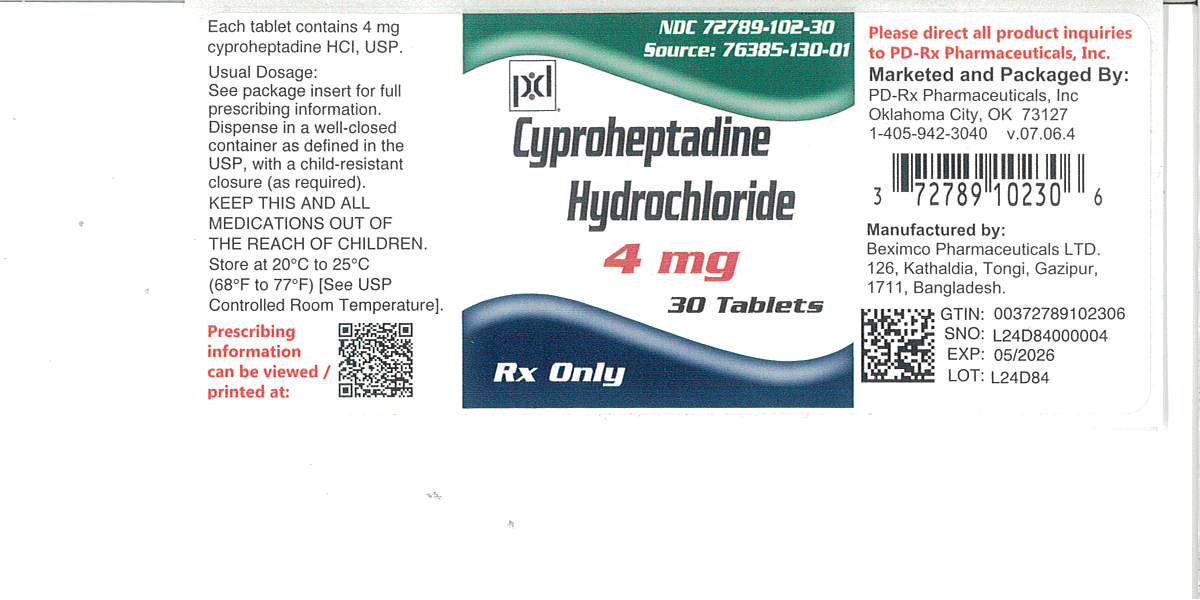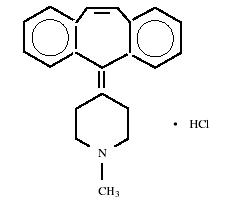 DRUG LABEL: Cyproheptadine Hydrochloride
NDC: 72789-102 | Form: TABLET
Manufacturer: PD-Rx Pharmaceuticals, Inc.
Category: prescription | Type: HUMAN PRESCRIPTION DRUG LABEL
Date: 20260216

ACTIVE INGREDIENTS: CYPROHEPTADINE HYDROCHLORIDE 4 mg/1 1
INACTIVE INGREDIENTS: LACTOSE MONOHYDRATE; MAGNESIUM STEARATE; CELLULOSE, MICROCRYSTALLINE; SODIUM STARCH GLYCOLATE TYPE A POTATO

CYPROHEPTADINE HYDROCHLORIDE TABLETS USP
Rx only

DESCRIPTION

Cyproheptadine HCl, is an antihistaminic and antiserotonergic agent. Cyproheptadine hydrochloride, USP is a white to slightly yellowish crystalline solid, with a molecular weight of 350.89, which is soluble in water, freely soluble in methanol, sparingly soluble in ethanol, soluble in chloroform, and practically insoluble in ether. It is the sesquihydrate 4-(5H-dibenzo[a,d]cyclohepten-5-ylidene)-1-methylpiperidine hydrochloride. The molecular formula of the anhydrous salt is C21H21N•HCl and the structural formula of the anhydrous salt is as follows:

C21H21N• HCl M.W. 350.89

Cyproheptadine hydrochloride, USP is available for oral administration in 4 mg tablets. Each tablet contains: Inactives:Lactose Monohydrate, Microcrystalline Cellulose, Sodium Starch Glycolate and Magnesium Stearate.

CLINICAL PHARMACOLOGY

Cyproheptadine is a serotonin and histamine antagonist with anticholinergic and sedative effects. Antiserotonin and antihistamine drugs appear to compete with serotonin and histamine, respectively, for receptor sites.

Pharmacokinetics and Metabolism

After a single 4 mg oral dose of^14C-labelled cyproheptadine HCl in normal subjects, given as tablets, 2 to 20% of the radioactivity was excreted in the stools. Only about 34% of the stool radioactivity was unchanged drug, corresponding to less than 5.7% of the dose. At least 40% of the administered radioactivity was excreted in the urine. No detectable amounts of unchanged drug were present in the urine of patients on chronic 12 to 20 mg daily doses. The principle metabolite found in human urine has been identified as a quaternary ammonium glucuronide conjugate of cyproheptadine. Elimination is diminished in renal insufficiency.

INDICATIONS AND USAGE

Perennial and seasonal allergic rhinitis
Vasomotor rhinitisAllergic conjunctivitis due to inhalant allergens and foodsMild, uncomplicated allergic skin manifestations of urticaria and angioedema.Amelioration of allergic reactions to blood or plasmaCold urticariaDermatographism

As therapy for anaphylactic reactions adjunctive to epinephrine and other standard measures after the acute manifestations have been controlled.

CONTRAINDICATIONS

Newborn or Premature Infants

This drug should notbe used in newborn or premature infants.

Nursing Mothers

Because of the higher risk of antihistamines for infants generally and for newborns and prematures in particular, antihistamine therapy is contraindicated in nursing mothers.

Other Conditions

Hypersensitivity to cyproheptadine and other drugs of similar chemical structure.
Monoamine oxidase inhibitor therapy (See DRUG INTERACTIONS.)Angle-closure glaucomaStenosing peptic ulcerSymptomatic prostatic hypertrophyBladder neck obstructionPyloroduodenal obstructionElderly, debilitated patients

WARNINGS

Pediatric Patients

Overdosage of antihistamines, particularly in infants and young children, may produce hallucinations, central nervous system depression, convulsions, respiratory and cardiac arrest, and death. Antihistamines may diminish mental alertness; conversely, particularly, in the young child, they may occasionally produce excitation.

CNS Depressants

Antihistamines may have additive effects with alcohol and other CNS depressants, e.g., hypnotics, sedatives, tranquilizers, antianxiety agents.

Activities Requiring Mental Alertness

Patients should be warned about engaging in activities requiring mental alertness and motor coordination, such as driving a car or operating machinery.

Antihistamines are more likely to cause dizziness, sedation, and hypotension in elderly patients (see PRECAUTIONS, Geriatric Use).

PRECAUTIONS

General

Cyproheptadine has an atropine-like action and, therefore, should be used with caution in patients with:
History of bronchial asthmaIncreased intraocular pressureHyperthyroidismCardiovascular diseaseHypertension

Information for Patients

Antihistamines may diminish mental alertness; conversely, particularly, in the young child, they may occasionally produce excitation. Patients should be warned about engaging in activities requiring mental alertness and motor coordination, such as driving a car or operating machinery.

Drug Interactions

MAO inhibitors prolong and intensify the anticholinergic effects of antihistamines.

Antihistamines may have additive effects with alcohol and other CNS depressants, e.g., hypnotics, sedatives, tranquilizers, antianxiety agents.

Carcinogenesis, Mutagenesis, Impairment of Fertility

Long-term carcinogenic studies have not been done with cyproheptadine.

Cyproheptadine had no effect on fertility in a two-litter study in rats or a two generation study in mice at about 10 times the human dose.

Cyproheptadine did not produce chromosome damage in human lymphocytes or fibroblasts in vitro; high doses (10^-4M) were cytotoxic. Cyproheptadine did not have any mutagenic effect in the Ames microbial mutagen test; concentrations of above 500 mcg/plate inhibited bacterial growth.

Pregnancy

Pregnancy Category B

Reproduction studies have been performed in rabbits, mice, and rats at oral or subcutaneous doses up to 32 times the maximum recommended human oral dose and have revealed no evidence of impaired fertility or harm to the fetus due to cyproheptadine. Cyproheptadine has been shown to be fetotoxic in rats when given by intraperitoneal injection in doses four times the maximum recommended human oral dose. Two studies in pregnant women, however, have not shown that cyproheptadine increases the risk of abnormalities when administered during the first, second and third trimesters of pregnancy. No teratogenic effects were observed in any of the newborns. Nevertheless, because the studies in humans cannot rule out the possibility of harm, cyproheptadine should be used during pregnancy only if clearly needed.

Nursing Mothers

It is not known whether this drug is excreted in human milk. Because many drugs are excreted in human milk, and because of the potential for serious adverse reactions in nursing infants from cyproheptadine, a decision should be made whether to discontinue nursing or to discontinue the drug, taking into account the importance of the drug to the mother (see CONTRAINDICATIONS).

Pediatric Use

Safety and effectiveness in pediatric patients below the age of two have not been established (see CONTRAINDICATIONS, Newborn or Premature Infants, and WARNINGS, Pediatric Patients).

Geriatric Use

Clinical studies of cyproheptadine HCl tablets did not include sufficient numbers of subjects aged 65 and over to determine whether they respond differently from younger subjects. Other reported clinical experience has not identified differences in responses between the elderly and younger patients. In general, dose selection for an elderly patient should be cautious, usually starting at the low end of the dosing range, reflecting the greater frequency of decreased hepatic, renal, or cardiac function, and of concomitant disease or other drug therapy (see WARNINGS, Activities Requiring Mental Alertness).

ADVERSE REACTIONS

Adverse reactions which have been reported with the use of antihistamines are as follows:

Central Nervous System

Sedation and sleepiness (often transient), dizziness, disturbed coordination, confusion, restlessness, excitation, nervousness, tremor, irritability, insomnia, paresthesias, neuritis, convulsions, euphoria, hallucinations, hysteria, faintness.

Integumentary

Allergic manifestation of rash and edema, excessive perspiration, urticaria, photosensitivity.

Special Senses

Acute labyrinthitis, blurred vision, diplopia, vertigo, tinnitus.

Cardiovascular

Hypotension, palpitation, tachycardia, extrasystoles, anaphylactic shock.

Hematologic

Hemolytic anemia, leukopenia, agranulocytosis, thrombocytopenia.

Digestive System

Cholestasis, hepatic failure, hepatitis, hepatic function abnormality, dryness of mouth, epigastric distress, anorexia, nausea, vomiting, diarrhea, constipation, jaundice.

Genitourinary

Urinary frequency, difficult urination, urinary retention, early menses.

Respiratory

Dryness of nose and throat, thickening of bronchial secretions, tightness of chest and wheezing, nasal stuffiness.

Miscellaneous

Fatigue, chills, headache, increased appetite/weight gain.

OVERDOSAGE

Antihistamine overdosage reactions may vary from central nervous system depression to stimulation especially in pediatric patients. Also, atropine-like signs and symptoms (dry mouth; fixed, dilated pupils; flushing, etc.) as well as gastrointestinal symptoms may occur.

If vomiting has not occurred spontaneously, the patient should be induced to vomit with syrup of ipecac.

If patient is unable to vomit, perform gastric lavage followed by activated charcoal. Isotonic or ½ isotonic saline is the lavage of choice. Precautions against aspiration must be taken especially in infants and children.

When life threatening CNS signs and symptoms are present, intravenous physostigmine salicylate may be considered. Dosage and frequency of administration are dependent on age, clinical response, and recurrence after response. (See package circulars for physostigmine products.)

Saline cathartics, as milk of magnesia, by osmosis draw water into the bowel and, therefore, are valuable for their action in rapid dilution of bowel content.

Stimulants should not be used.

Vasopressors may be used to treat hypotension.

The oral LD50of cyproheptadine is 123 mg/kg, and 295 mg/kg in the mouse and rat, respectively.

DOSAGE AND ADMINISTRATION

DOSAGE SHOULD BE INDIVIDUALIZED ACCORDING TO THE NEEDS AND THE RESPONSE OF THE PATIENT.

Each tablet contains 4 mg of cyproheptadine hydrochloride.

Pediatric Patients

Age 2 to 6 years

The total daily dosage for pediatric patients may be calculated on the basis of body weight or body area using approximately 0.25 mg/kg/day or 8 mg per square meter of body surface (8 mg/m^2).

The usual dose is 2 mg (½ tablet) two or three times a day, adjusted as necessary to the size and response of the patient. The dose is not to exceed 12 mg a day.

Age 7 to 14 years

The usual dose is 4 mg (1 tablet) two or three times a day adjusted as necessary to the size and response of the patient. The dose is not to exceed 16 mg a day.

Adults

The total daily dose for adults should not exceed 0.5 mg/kg/day. The therapeutic range is 4 to 20 mg a day, with the majority of patients requiring 12 to 16 mg a day. An occasional patient may require as much as 32 mg a day for adequate relief. It is suggested that dosage be initiated with 4 mg (1 tablet) three times a day and adjusted according to the size and response of the patient.

HOW SUPPLIED

Cyproheptadine hydrochloride tablets USP, 4 mg are available as white to off-white color, round flat face tablet with debossed “B137” on one side and scored on the other, containing 4 mg of cyproheptadine HCl packaged in bottles of :

PHARMACIST: Dispense in a well-closed container as defined in the USP, with a child-resistant closure (as required).

Bottles of 30 tablets: NDC 72789-102-30
Bottles of 100 tablets: NDC 72789-102-01

STORAGE

Store at 20° to 25°C (68° to 77°F) [See USP Controlled Room Temperature.]

To report SUSPECTED ADVERSE REACTIONS, contact FDA at 1-800-FDA-1088 or www.fda.gov/medwatch.

PRINCIPAL DISPLAY PANEL - 4 mg Label Text

Rx only

Cyproheptadine Hydrochloride Tablets USP, 4 mg